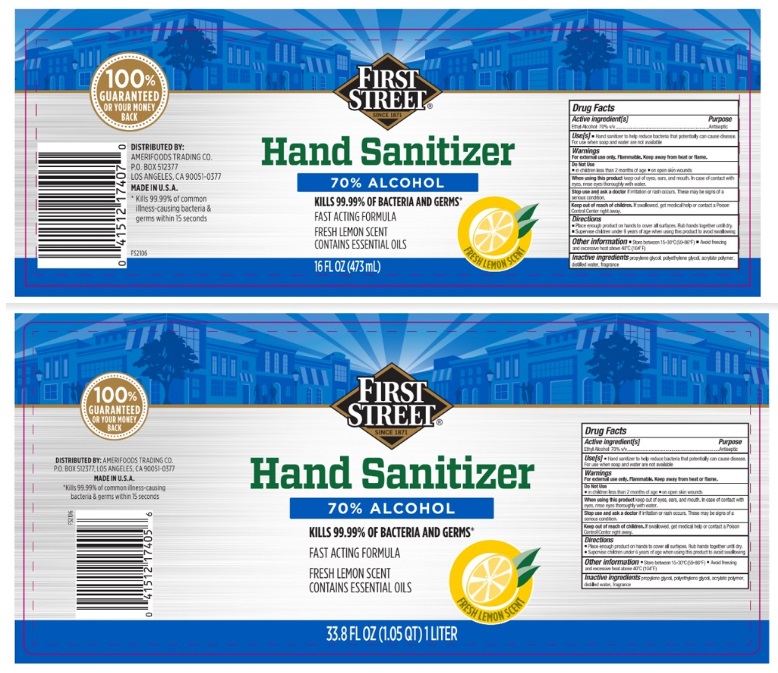 DRUG LABEL: First Street Hand Sanitizer fresh lemon
NDC: 59860-002 | Form: LIQUID
Manufacturer: SMART & FINAL STORES LLC
Category: otc | Type: HUMAN OTC DRUG LABEL
Date: 20251007

ACTIVE INGREDIENTS: ALCOHOL 70 mL/100 mL
INACTIVE INGREDIENTS: PROPYLENE GLYCOL; POLYETHYLENE GLYCOL, UNSPECIFIED; WATER; RAPIDGEL EZ1

Active Ingredient

Ethyl Alcohol 70% V/V

Purpose

Antiseptic

Use

Hand sanitizer to help reduce bacteria that potentially can cause disease

For use when soap and water are not available

Warnings

For external use only. Flammable. Keep away from heat or flame

Do not use on

- children less than 2 months of age
- Do not use on open skin wounds

When using this productkeep out of eyes, ears and mouth. In case of contact with eyes, rinse eyes thoroughly with water.

Stop use and ask a doctorif irritation or rash occurs. These may be signs of a serious condition.

Keep out of reach of children. If swallowed, get medical help or contact a Poison Control Center right away.

Directions

- Place enough product on hands to cover all surfaces. Rub hands together until dry.
- Supervise children under 6 years of age when using this product to avoid swallowing.

Other information

- Store between 15°-30°C (59°-86°F)
- Avoid freezing and excessive heat above 40°C (104°F)

Inactive ingredients

Propylene glycol, polyethylene glycol, water, acrylate polymer, fragrance.